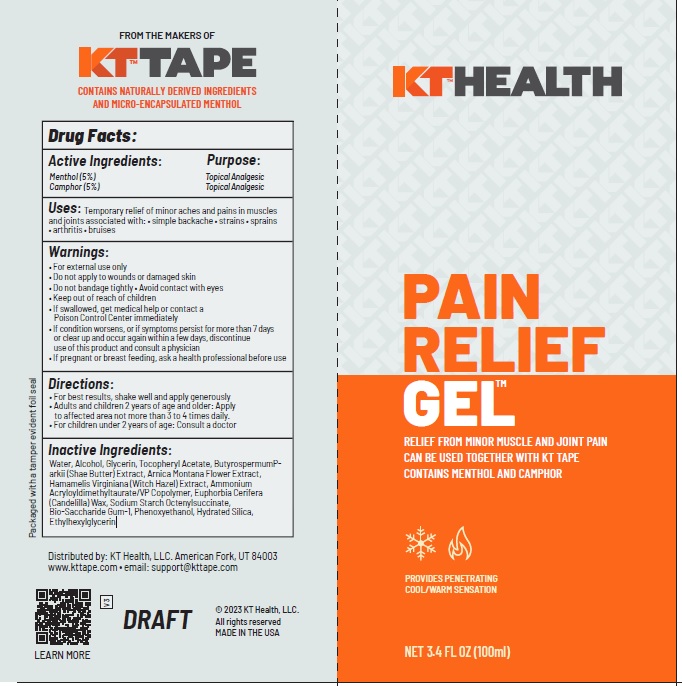 DRUG LABEL: KT Recovery Plus Pain Relief Gel
NDC: 73044-103 | Form: GEL
Manufacturer: KT Health LLC
Category: otc | Type: HUMAN OTC DRUG LABEL
Date: 20241118

ACTIVE INGREDIENTS: MENTHOL 5 g/100 mL; CAMPHOR (NATURAL) 5 g/100 mL
INACTIVE INGREDIENTS: WATER; ALCOHOL; GLYCERIN; .ALPHA.-TOCOPHEROL ACETATE; SHEANUT; ARNICA MONTANA FLOWER; HAMAMELIS VIRGINIANA TOP; AMMONIUM ACRYLOYLDIMETHYLTAURATE/VP COPOLYMER; CANDELILLA WAX; OCTENYLSUCCINIC ACID; BIOSACCHARIDE GUM-1; PHENOXYETHANOL; HYDRATED SILICA; ETHYLHEXYLGLYCERIN

Active Ingredients Purpose

Camphor (5%) Topical Analgesic
Menthol (5%) Topical Analgesic

Uses

Temporary relief of minor aches and pains in muscles and joints associated with: • simple backache • strains • sprains
• arthritis • bruises

Warnings

• For external use only
• Do not apply to wounds or damaged skin
• Do not bandage tightly • Avoid contact with eyes
• Keep out of reach of children
• If swallowed, get medical help or contact a Poison Control Center immediately
• If condition worsens, or if symptoms persist for more than 7 days or clear up and occur again within a few days, discontinue use of this product and consult a physician
• If pregnant or breast feeding, ask a health professional before use

Directions

• For best results, shake well and apply generously
• Adults and children 2 years of age and older: Apply to affected area not more than 3 to 4 times daily.
• For children under 2 years of age: Consult a doctor

INACTIVE INGREDIENT

Water, Alcohol, Glycerin, Tocopheryl Acetate, ButyrospermumParkii (Shae Butter) Extract, Arnica Montana Flower Extract, Hamamelis Virginiana (Witch Hazel) Extract, Ammonium Acryloyldimethyltaurate/VP Copolymer, Euphorbia Cerifera (Candelilla) Wax, Sodium Starch Octenylsuccinate,
Bio-Saccharide Gum-1, Phenoxyethanol, Hydrated Silica, Ethylhexylglycerin